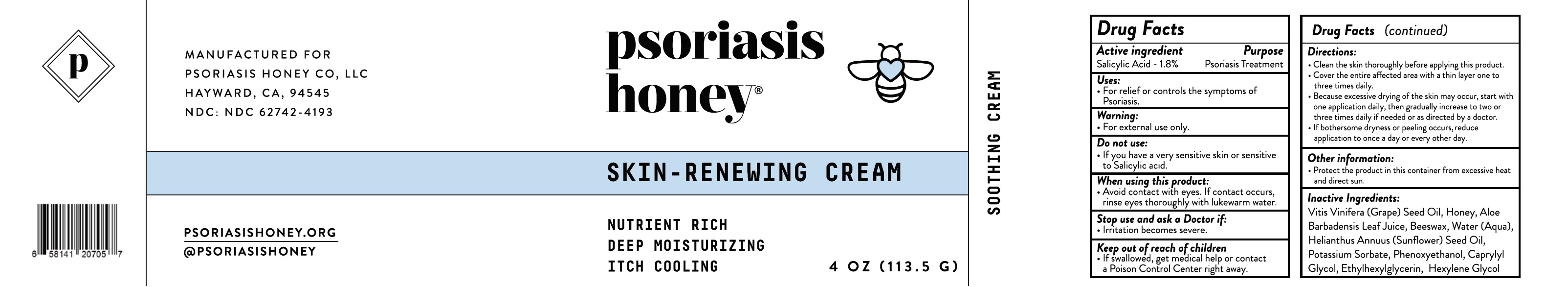 DRUG LABEL: Skin Renewing Cream
NDC: 62742-4193 | Form: CREAM
Manufacturer: Allure Labs
Category: otc | Type: HUMAN OTC DRUG LABEL
Date: 20241209

ACTIVE INGREDIENTS: SALICYLIC ACID 1.8 mg/1 g
INACTIVE INGREDIENTS: SUNFLOWER OIL; PHENOXYETHANOL; HEXYLENE GLYCOL; YELLOW WAX; POTASSIUM SORBATE; ETHYLHEXYLGLYCERIN; WATER; CAPRYLYL GLYCOL; GRAPE SEED OIL; HONEY; ALOE VERA LEAF

Drug Facts

Active Ingredients:

Salicylic Acid 1.8%

Purpose: Psoriasis Treatment

Uses:

- For relief or controls the symptoms of Psoriasis.

WARNINGS

Warning: For external use only.

Do not use if you have a very sensitive skin or sensitive to salicylic acid.

Stop use and ask a doctor: If irritation becomes severe.

When using this product - avoid contact with eyes. If contactc occurs, rinse eyes thoroughly with lukewarm water.

Keep out of reach of children: If swallowed, get medical help or contact a Poison Control Center right away.

Directions:

- Clean the skin thoroughly before applying this product
- Cover the entire affected area with a thin layer one to three times daily.
- Because excessive drying of the skin may occur, start with one application daily, then gradually increase to two or three times daily if needed or as directed by a doctor.
- If bothersome dryness or peeling occurs, reduce application to once a day or evert other day.

Other Information: Protect the product in this container from excessive heat and direct sun.

INACTIVE INGREDIENT

Inactive Ingredients: Vitis Vinifera (Grape) Seed Oil, Honey, Aloe Barbadensis Leaf juice, Beeswax, Water (Aqua), Potassium Sorbate, Helianthus Annus (Sunflower) Seed Oil, Phenoxyethanol, Caprylyl Glycol, Ethylhexylglycerin, Hexylene Glycol.

PACKAGE LABEL

Manufactured For

Psoriasis Honey CO LLC.

Hayward, CA, 94545